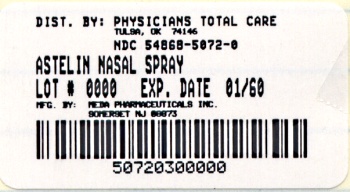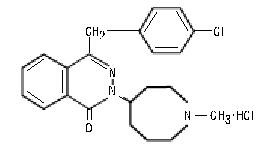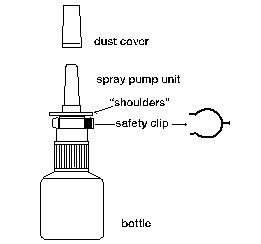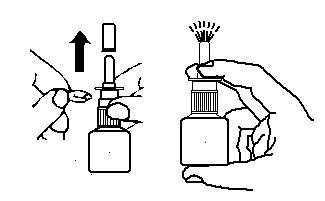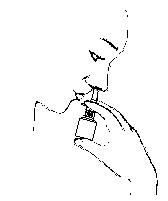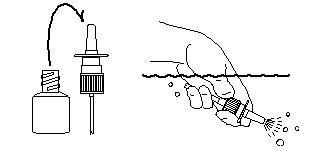 DRUG LABEL: Astelin
NDC: 54868-5072 | Form: SPRAY, METERED
Manufacturer: Physicians Total Care, Inc.
Category: prescription | Type: HUMAN PRESCRIPTION DRUG LABEL
Date: 20100518

ACTIVE INGREDIENTS: AZELASTINE HYDROCHLORIDE 137 ug/1 1
INACTIVE INGREDIENTS: BENZALKONIUM CHLORIDE 125 ug/1 1

ASTELIN®
(azelastine hydrochloride)
Nasal Spray, 137 mcg
IN-023S6-07 Rev. 1/09
For Intranasal Use Only

DESCRIPTION

Astelin® (azelastine hydrochloride) Nasal Spray, 137 micrograms (mcg), is an antihistamine formulated as a metered-spray solution for intranasal administration. Azelastine hydrochloride occurs as a white, almost odorless, crystalline powder with a bitter taste. It has a molecular weight of 418.37. It is sparingly soluble in water, methanol, and propylene glycol and slightly soluble in ethanol, octanol, and glycerine. It has a melting point of about 225°C and the pH of a saturated solution is between 5.0 and 5.4. Its chemical name is (±)-1-(2H)-phthalazinone,4-[(4-chlorophenyl) methyl]-2-(hexahydro-1-methyl-1H-azepin-4-yl)-, monohydrochloride. Its molecular formula is C22H24CIN3O•HCl with the following chemical structure:

Astelin® Nasal Spray contains 0.1% azelastine hydrochloride in an aqueous solution at pH 6.8 ± 0.3. It also contains benzalkonium chloride (125 mcg/mL), edetate disodium, hypromellose, citric acid, dibasic sodium phosphate, sodium chloride, and purified water.

After priming, each metered spray delivers a 0.137 mL mean volume containing 137 mcg of azelastine hydrochloride (equivalent to 125 mcg of azelastine base). The bottle can deliver 200 metered sprays.

CLINICAL PHARMACOLOGY

Azelastine hydrochloride, a phthalazinone derivative, exhibits histamine H1 -receptor antagonist activity in isolated tissues, animal models, and humans. Astelin® Nasal Spray is administered as a racemic mixture with no difference in pharmacologic activity noted between the enantiomers in in vitro studies. The major metabolite, desmethylazelastine, also possesses H1 -receptor antagonist activity.

Pharmacokinetics and Metabolism

After intranasal administration, the systemic bioavailability of azelastine hydrochloride is approximately 40%. Maximum plasma concentrations (Cmax) are achieved in 2-3 hours. Based on intravenous and oral administration, the elimination half-life, steady-state volume of distribution, and plasma clearance are 22 hours, 14.5 L/kg, and 0.5 L/h/kg, respectively. Approximately 75% of an oral dose of radiolabeled azelastine hydrochloride was excreted in the feces with less than 10% as unchanged azelastine. Azelastine is oxidatively metabolized to the principal active metabolite, desmethylazelastine, by the cytochrome P450 enzyme system. The specific P450 isoforms responsible for the biotransformation of azelastine have not been identified; however, clinical interaction studies with the known CYP3A4 inhibitor erythromycin failed to demonstrate a pharmacokinetic interaction. In a multiple-dose, steady-state drug interaction study in normal volunteers, cimetidine (400 mg twice daily), a nonspecific P450 inhibitor, raised orally administered mean azelastine (4 mg twice daily) concentrations by approximately 65%.

The major active metabolite, desmethylazelastine, was not measurable (below assay limits) after single-dose intranasal administration of azelastine hydrochloride. After intranasal dosing of azelastine hydrochloride to steady-state, plasma concentrations of desmethylazelastine range from 20-50% of azelastine concentrations. When azelastine hydrochloride is administered orally, desmethylazelastine has an elimination half-life of 54 hours. Limited data indicate that the metabolite profile is similar when azelastine hydrochloride is administered via the intranasal or oral route.

In vitro studies with human plasma indicate that the plasma protein binding of azelastine and desmethylazelastine are approximately 88% and 97%, respectively.

Azelastine hydrochloride administered intranasally at doses above two sprays per nostril twice daily for 29 days resulted in greater than proportional increases in Cmax and area under the curve (AUC) for azelastine.

Studies in healthy subjects administered oral doses of azelastine hydrochloride demonstrated linear responses in Cmax and AUC.

Special Populations

Following oral administration, pharmacokinetic parameters were not influenced by age, gender, or hepatic impairment.

Based on oral, single-dose studies, renal insufficiency (creatinine clearance <50 mL/min) resulted in a 70-75% higher Cmax and AUC compared to normal subjects. Time to maximum concentration was unchanged.

Oral azelastine has been safely administered to over 1400 asthmatic subjects, supporting the safety of administering Astelin® Nasal Spray to allergic rhinitis patients with asthma.

Pharmacodynamics

In a placebo-controlled study (95 subjects with allergic rhinitis), there was no evidence of an effect of Astelin® Nasal Spray (2 sprays per nostril twice daily for 56 days) on cardiac repolarization as represented by the corrected QT interval (QTc) of the electrocardiogram. At higher oral exposures (≥4 mg twice daily), a nonclinically significant mean change on the QTc (3-7 millisecond increase) was observed.

Interaction studies investigating the cardiac repolarization effects of concomitantly administered oral azelastine hydrochloride and erythromycin or ketoconazole were conducted. Oral erythromycin had no effect on azelastine pharmacokinetics or QTc based on analysis of serial electrocardiograms. Ketoconazole interfered with the measurement of azelastine plasma levels; however, no effects on QTc were observed (see PRECAUTIONS, Drug Interactions).

Clinical Trials

Seasonal Allergic Rhinitis

Trials Supporting Two Sprays Per Nostril Twice Daily

U.S. placebo-controlled clinical trials of Astelin® Nasal Spray included 322 patients with seasonal allergic rhinitis who received two sprays per nostril twice a day for up to 4 weeks. These trials included 55 pediatric patients ages 12 to 16 years. Astelin® Nasal Spray showed significant improvement compared to placebo in the two primary efficacy variables- the Total Symptom Complex (TSC) and the Major Symptom Complex (MSC).The results for the MSC are shown in Table 1 as the mean change from Baseline in the average of individual symptoms of nose blows, sneezes, runny nose/sniffles, itchy nose, and watery eyes as assessed by patients on a 0-5 categorical scale.

Table 1: Summary of Primary Efficacy* Analyses for Pivotal Studies Supporting Two Sprays Per Nostril Twice Daily.

 | Astelin® Nasal Spray | Placebo | Outcomes
 | Astelin® Nasal Spray | Placebo | Astelin® vs. Placebo
 | Mean (SD) |  | Difference between Treatments | P value
Study 26: 12 Hour AM and PM Reflective MSC
Sample Size | N=63 | N=60
Baseline | 11.48 (4.13) | 10.84 (4.53)
Change from Baseline | -3.05 (3.51) | -1.07 (3.52) | 1.98 | 0.0024
Study 31: 12 Hour AM and PM Reflective MSC
Sample Size | N=63 | N=63
Baseline | 12.50 (4.5) | 12.18 (4.64)
Change from Baseline | -4.10 (3.46) | -2.07 (4.01) | 2.03 | 0.0023
Study 33: 12 Hour AM and PM Reflective MSC
Sample Size | N=66 | N=66
Baseline | 12.04 (4.03) | 11.66 (3.96)
Change from Baseline | -3.31 (3.74) | -1.96 (3.57) | 1.35 | 0.0374
* Average of individual symptoms of nose blows, sneezes, runny nose/sniffles, itchy nose, and watery eyes as assessed by patients on a 0-5 categorical scale.

Trials Supporting One Spray Per Nostril Twice Daily

Two hundred seventy five patients with seasonal allergic rhinitis received Astelin® Nasal Spray one spray per nostril twice daily for 2 weeks in two U.S. placebo-controlled trials. The primary efficacy endpoint was the change from Baseline to Day 14 in the Total Nasal Symptom Score [TNSS] (the average of individual scores of runny nose, sneezing, itchy nose, and nasal congestion) as assessed by patients on a 0-3 categorical scale. Compared to placebo, Astelin® Nasal Spray significantly improved the TNSS. The results are shown in Table 2.

Table 2: Summary of Primary Efficacy* Analyses for Pivotal Studies Supporting One Spray Per Nostril Twice Daily.

 | Astelin® Nasal Spray | Placebo | Outcomes
 | Astelin® Nasal Spray | Placebo | Astelin® vs. Placebo
 | LS Mean (SD) |  | Difference between Treatments | P value
Study 419: 12 Hour AM and PM Reflective TNSS
Sample Size | N=138 | N=141
Baseline | 16.34 (4.222) | 17.21 (4.316)
Change from Baseline | -2.69 (4.789) | -1.31 (4.285) | 1.38 | 0.0017
Study 420: 12 Hour AM and PM Reflective TNSS
Sample Size | N=137 | N=136
Baseline | 16.62 (4.197) | 16.84 (4.768)
Change from Baseline | -3.68 (4.163) | -2.50 (4.011) | 1.18 | 0.0173
* Average of individual symptoms of runny nose, sneezing, itchy nose, and nasal congestion as assessed by patients on a 0-3 categorical scale.

Two-week studies comparing the efficacy (and safety) of Astelin® Nasal Spray two sprays per nostril twice daily versus one spray per nostril twice daily were not conducted.

Other Supporting Studies

In dose-ranging trials, administration of Astelin® Nasal Spray, two sprays per nostril twice daily, resulted in a decrease in symptoms, which reached statistical significance from saline placebo within 3 hours after initial dosing and persisted over the 12-hour dosing interval.

There were no findings on nasal examination in an 8-week study that suggested any adverse effect of azelastine on the nasal mucosa.

Vasomotor Rhinitis

Two hundred sixteen patients with vasomotor rhinitis received Astelin® Nasal Spray two sprays per nostril twice a day in two U.S. placebo controlled trials. These patients had vasomotor rhinitis for at least one year, negative skin tests to indoor and outdoor aeroallergens, negative nasal smears for eosinophils, and negative sinus X-rays, Astelin® Nasal Spray significantly improved a symptom complex comprised of rhinorrhea, post nasal drip, nasal congestion, and sneezing.

INDICATIONS AND USAGE

Astelin® Nasal Spray is indicated for the treatment of the symptoms of seasonal allergic rhinitis such as rhinorrhea, sneezing, and nasal pruritus in adults and children 5 years and older, and for the treatment of the symptoms of vasomotor rhinitis, such as rhinorrhea, nasal congestion and postnasal drip in adults and children 12 years and older.

CONTRAINDICATIONS

Astelin® Nasal Spray is contraindicated in patients with a known hypersensitivity to azelastine hydrochloride or any of its components.

PRECAUTIONS

Activities Requiring Mental Alertness: In clinical trials, the occurrence of somnolence has been reported in some patients taking Astelin® Nasal Spray; due caution should therefore be exercised when driving a car or operating potentially dangerous machinery while using Astelin® Nasal Spray. Concurrent use of Astelin® Nasal Spray with alcohol or other CNS depressants should be avoided because additional reductions in alertness and additional impairment of CNS performance may occur.

PATIENT COUNSELING INFORMATION

Information for Patients: Patients should be instructed to use Astelin® Nasal Spray only as prescribed. For the proper use of the nasal spray and to attain maximum improvement, the patient should read and follow carefully the accompanying patient instructions. Patients should be instructed to prime the delivery system before initial use and after storage for 3 or more days (see PATIENT INSTRUCTIONS FOR USE). Patients should also be instructed to store the bottle upright at room temperature with the pump tightly closed and out of the reach of children. In case of accidental ingestion by a young child, seek professional assistance or contact a poison control center immediately.

Patients should be advised against the concurrent use of Astelin® Nasal Spray with other antihistamines without consulting a physician. Patients who are, or may become, pregnant should be told that this product should be used in pregnancy or during lactation only if the potential benefit justifies the potential risks to the fetus or nursing infant. Patients should be advised to assess their individual responses to Astelin® Nasal Spray before engaging in any activity requiring mental alertness, such as driving a car or operating machinery. Patients should be advised that the concurrent use of Astelin® Nasal Spray with alcohol or other CNS depressants may lead to additional reductions in alertness and impairment of CNS performance and should be avoided (see Drug Interactions).

DRUG INTERACTIONS

Drug Interactions: Concurrent use of Astelin® Nasal Spray with alcohol or other CNS depressants should be avoided because additional reductions in alertness and additional impairment of CNS performance may occur.

Cimetidine (400 mg twice daily) increased the mean Cmax and AUC of orally administered azelastine hydrochloride (4 mg twice daily) by approximately 65%. Ranitidine hydrochloride (150 mg twice daily) had no effect on azelastine pharmacokinetics.

Interaction studies investigating the cardiac effects, as measured by the corrected QT interval (QTc), of concomitantly administered oral azelastine hydrochloride and erythromycin or ketoconazole were conducted. Oral erythromycin (500 mg three times daily for seven days) had no effect on azelastine pharmacokinetics or QTc based on analyses of serial electrocardiograms. Ketoconazole (200 mg twice daily for seven days) interfered with the measurement of azelastine plasma concentrations; however, no effects on QTc were observed.

No significant pharmacokinetic interaction was observed with the coadministration of an oral 4 mg dose of azelastine hydrochloride twice daily and theophylline 300 mg or 400 mg twice daily.

CARCINOGENESIS AND MUTAGENESIS AND IMPAIRMENT OF FERTILITY

Carcinogenesis, Mutagenesis, Impairment of Fertility: In 2 year carcinogenicity studies in rats and mice azelastine hydrochloride did not show evidence of carcinogenicity at oral doses up to 30 mg/kg and 25 mg/kg, respectively (approximately 240 and 100 times the maximum recommended daily intranasal dose in adults and children on a mg/m^2 basis).

Azelastine hydrochloride showed no genotoxic effects in the Ames test, DNA repair test, mouse lymphoma forward mutation assay, mouse micronucleus test, or chromosomal aberration test in rat bone marrow.

Reproduction and fertility studies in rats showed no effects on male or female fertility at oral doses up to 30 mg/kg (approximately 240 times the maximum recommended daily intranasal dose in adults on a mg/m^2 basis). At 68.6 mg/kg (approximately 560 times the maximum recommended daily intranasal dose in adults on a mg/m^2 basis), the duration of estrous cycles was prolonged and copulatory activity and the number of pregnancies were decreased. The numbers of corpora lutea and implantations were decreased; however, pre-implantation loss was not increased.

PREGNANCY

Pregnancy Category C: Azelastine hydrochloride has been shown to cause developmental toxicity. Treatment of mice with an oral dose of 68.6 mg/kg (approximately 280 times the maximum recommended daily intranasal dose in adults on a mg/m^2 basis) caused embryo-fetal death, malformations (cleft palate; short or absent tail; fused, absent or branched ribs), delayed ossification and decreased fetal weight. This dose also caused maternal toxicity as evidenced by decreased body weight. Neither fetal nor maternal effects occurred at a dose of 3 mg/kg (approximately 10 times the maximum recommended daily intranasal dose in adults on a mg/m^2 basis).

In rats, an oral dose of 30 mg/kg (approximately 240 times the maximum recommended daily intranasal dose in adults on a mg/m^2 basis) caused malformations (oligo-and brachydactylia), delayed ossification and skeletal variations, in the absence of maternal toxicity. At 68.6 mg/kg (approximately 560 times the maximum recommended daily intranasal dose in adults on a mg/m^2 basis) azelastine hydrochloride also caused embryo-fetal death and decreased fetal weight; however, the 68.6 mg/kg dose caused severe maternal toxicity. Neither fetal nor maternal effects occurred at a dose of 3 mg/kg (approximately 25 times the maximum recommended daily intranasal dose in adults on a mg/m^2 basis).

In rabbits, oral doses of 30 mg/kg and greater (approximately 500 times the maximum recommended daily intranasal dose in adults on a mg/m^2 basis) caused abortion, delayed ossification and decreased fetal weight; however, these doses also resulted in severe maternal toxicity. Neither fetal nor maternal effects occurred at a dose of 0.3 mg/kg (approximately 5 times the maximum recommended daily intranasal dose in adults on a mg/m^2 basis).

There are no adequate and well-controlled clinical studies in pregnant women. Astelin® Nasal Spray should be used during pregnancy only if the potential benefit justifies the potential risk to the fetus.

NURSING MOTHERS

Nursing Mothers: It is not known whether azelastine hydrochloride is excreted in human milk. Because many drugs are excreted in human milk, caution should be exercised when Astelin® Nasal Spray is administered to a nursing woman.

PEDIATRIC USE

Pediatric Use: The safety and effectiveness of Astelin® Nasal Spray at a dose of 1 spray per nostril twice daily has been established for patients 5 through 11 years of age for the treatment of symptoms of seasonal allergic rhinitis. The safety of this dosage of Astelin® Nasal Spray was established in well-controlled studies of this dose in 176 patients 5 to 12 years of age treated for up to 6 weeks. The efficacy of Astelin® Nasal Spray at this dose is based on an extrapolation of the finding of efficacy in adults, on the likelihood that the disease course, pathophysiology and response to treatment are substantially similar in children compared to adults, and on supportive data from controlled clinical trials in patients 5 to 12 years of age at the dose of 1 spray per nostril twice daily. The safety and effectiveness of Astelin® Nasal Spray in patients below the age of 5 years have not been established.

GERIATRIC USE

Geriatric Use: Clinical studies of Astelin® Nasal Spray did not include sufficient numbers of subjects aged 65 and over to determine whether they respond differently from younger subjects. Other reported clinical experience has not identified differences in responses between the elderly and younger patients. In general, dose selection for an elderly patient should be cautious, usually starting at the low end of the dosing range, reflecting the greater frequency of decreased hepatic, renal, or cardiac function, and of concomitant disease or other drug therapy.

ADVERSE REACTIONS

To report SUSPECTED ADVERSE REACTIONS, contact Meda Pharmaceuticals Inc. at 1-800-526-3840 or FDA at 1-800-FDA-1088 or www.fda.gov/medwatch.

Seasonal Allergic Rhinitis

Astelin® Nasal Spray Two Sprays Per Nostril Twice Daily

Adverse experience information for Astelin® Nasal Spray is derived from six well-controlled, 2-day to 8-week clinical studies which included 391 patients who received Astelin® Nasal Spray at a dose of 2 sprays per nostril twice daily. In placebo-controlled efficacy trials, the incidence of discontinuation due to adverse reactions in patients receiving Astelin® Nasal Spray was not different from vehicle placebo (2.2% vs 2.8%, respectively). In these clinical studies, adverse events that occurred more often in patients treated with Astelin® Nasal Spray versus vehicle placebo included bitter taste (19.7% vs. 0.6%), somnolence (11.5% vs. 5.4%), weight increase (2.0% vs. 0%), and myalgia (1.5% vs. 0%).

The following table contains adverse events that were reported with frequencies ≥2% in the Astelin® Nasal Spray 2 sprays per nostril twice daily treatment group and more frequently than placebo in short-term (≤2 days) and long-term (2-8 weeks) clinical trials.

ADVERSE EVENT | Astelin® Nasal Spray n = 391 | Vehicle Placebo n = 353
Bitter Taste | 19.7 | 0.6
Headache | 14.8 | 12.7
Somnolence | 11.5 | 5.4
Nasal Burning | 4.1 | 1.7
Pharyngitis | 3.8 | 2.8
Dry Mouth | 2.8 | 1.7
Paroxysmal Sneezing | 3.1 | 1.1
Nausea | 2.8 | 1.1
Rhinitis | 2.3 | 1.4
Fatigue | 2.3 | 1.4
Dizziness | 2.0 | 1.4
Epistaxis | 2.0 | 1.4
Weight Increase | 2.0 | 0.0

Astelin® Nasal Spray One Spray Per Nostril Twice Daily

Adverse experience information for Astelin® Nasal Spray at a dose of one spray per nostril twice daily is derived from two placebo-controlled 2-week clinical studies which included 276 patients. None of the patients receiving Astelin® Nasal Spray were discontinued from these studies due to adverse reactions. Three patients receiving vehicle placebo were discontinued due to adverse reactions. Bitter taste was reported in 8.3% of patients compared to none in the placebo group. Somnolence was reported in 0.4% of patients compared to none in the placebo group.

A total of 176 patients 5 to 12 years of age were exposed to Astelin® Nasal Spray at a dose of 1 spray each nostril twice daily in 3 placebo-controlled studies. In these studies, adverse events that occurred more frequently in patients treated with Astelin® Nasal Spray than with placebo, and that were not represented in the adult adverse event table above include rhinitis/cold symptoms (17.0% vs 9.5%), cough (11.4% vs 8.3%), conjunctivitis (5.1% vs 1.8%), and asthma (4.5% vs 4.1%).

The following events were observed infrequently (<2% and exceeding placebo incidence) in patients who received Astelin® Nasal Spray dosed at 1 or 2 sprays per nostril twice daily in U.S. clinical trials.

Cardiovascular: flushing, hypertension, tachycardia.

Dermatological: contact dermatitis, eczema, hair and follicle infection, furunculosis, skin laceration.

Digestive: constipation, gastroenteritis, glossitis, ulcerative stomatitis, vomiting, increased SGPT, aphthous stomatitis, diarrhea, toothache.

Metabolic and Nutritional: increased appetite.

Musculoskeletal: myalgia, temporomandibular dislocation, rheumatoid arthritis.

Neurological: hyperkinesia, hypoesthesia, vertigo.

Psychological: anxiety, depersonalization, depression, nervousness, sleep disorder, thinking abnormal.

Respiratory: bronchospasm, coughing, throat burning, laryngitis, bronchitis, dry throat, nocturnal dyspnea, nasopharyngitis, nasal congestion, pharyngolaryngeal pain, sinusitis, nasal dryness, paranasal sinus hypersecretion, post nasal drip.

Special Senses: conjunctivitis, eye abnormality, eye pain, watery eyes, taste loss.

Urogenital: albuminuria, amenorrhea, breast pain, hematuria, increased urinary frequency.

Whole Body: allergic reaction, back pain, herpes simplex, viral infection, malaise, pain in extremities, abdominal pain, pyrexia.

ADVERSE REACTIONS

Vasomotor Rhinitis

Adverse experience information for Astelin® Nasal Spray is derived from two placebo-controlled clinical studies which included 216 patients who received Astelin® Nasal Spray at a dose of 2 sprays per nostril twice daily for up to 28 days. The incidence of discontinuation due to adverse reactions in patients receiving Astelin® Nasal Spray was not different from vehicle placebo (2.8% vs 2.9%, respectively).

The following adverse events were reported with frequencies ≥ 2% in the Astelin® Nasal Spray treatment group and more frequently than placebo.

ADVERSE EVENT | Astelin® Nasal Spray n = 216 | Vehicle Placebo n = 210
Bitter Taste | 19.4 | 2.4
Headache | 7.9 | 7.6
Dysesthesia | 7.9 | 3.3
Rhinitis | 5.6 | 2.4
Epistaxis | 3.2 | 2.4
Sinusitis | 3.2 | 1.9
Somnolence | 3.2 | 1.0

Events observed infrequently (<2% and exceeding placebo incidence) in patients who received Astelin® Nasal Spray (2 sprays/nostril twice daily) in U.S. clinical trials in vasomotor rhinitis were similar to those observed in U.S. clinical trials in seasonal allergic rhinitis.

In controlled trials involving nasal and oral azelastine hydrochloride formulations, there were infrequent occurrences of hepatic transaminase elevations. The clinical relevance of these reports has not been established.

In addition, the following spontaneous adverse events have been reported during the marketing of Astelin® Nasal Spray and causal relationship with the drug is unknown: anaphylactoid reaction, application site irritation, atrial fibrillation, chest pain, confusion, dyspnea, facial edema, involuntary muscle contractions, palpitations, paresthesia, parosmia, pruritus, rash, disturbance or loss of sense of smell and/or taste, tolerance, urinary retention, vision abnormal and xerophthalmia.

OVERDOSAGE

There have been no reported overdosages with Astelin® Nasal Spray. Acute overdosage by adults with this dosage form is unlikely to result in clinically significant adverse events, other than increased somnolence, since one bottle of Astelin® Nasal Spray contains 30 mg of azelastine hydrochloride. Clinical studies in adults with single doses of the oral formulation of azelastine hydrochloride (up to 16 mg) have not resulted in increased incidence of serious adverse events. General supportive measures should be employed if overdosage occurs. There is no known antidote to Astelin® Nasal Spray. Oral ingestion of antihistamines has the potential to cause serious adverse effects in young children. Accordingly, Astelin® Nasal Spray should be kept out of the reach of children. Oral doses of 120 mg/kg and greater (approximately 460 times the maximum recommended daily intranasal dose in adults and children on a mg/m^2 basis) were lethal in mice. Responses seen prior to death were tremor, convulsions, decreased muscle tone, and salivation. In dogs, single oral doses as high as 10 mg/kg (approximately 260 times the maximum recommended daily intranasal dose in adults and children on a mg/m^2 basis) were well tolerated, but single oral doses of 20 mg/kg were lethal.

DOSAGE AND ADMINISTRATION

Seasonal Allergic Rhinitis

The recommended dose of Astelin® Nasal Spray in adults and children 12 years and older with seasonal allergic rhinitis is one or two sprays per nostril twice daily. The recommended dose of Astelin® Nasal Spray in children 5 years to 11 years of age is one spray per nostril twice daily.

Vasomotor Rhinitis

The recommended dose of Astelin® Nasal Spray in adults and children 12 years and older with vasomotor rhinitis is two sprays per nostril twice daily.

Before initial use, the delivery system should be primed with 4 sprays or until a fine mist appears. When 3 or more days have elapsed since the last use, the pump should be reprimed with 2 sprays or until a fine mist appears.

CAUTION: Avoid spraying in the eyes.

Directions for Use: Illustrated patient instructions for proper use accompany each package of Astelin® Nasal Spray.

HOW SUPPLIED

Astelin® (azelastine hydrochloride) Nasal Spray, 137 mcg, (NDC 54868-5072-0) is supplied as a package containing 200 metered sprays in a high-density polyethylene (HDPE) bottle fitted with a metered-dose spray pump unit. Patient instructions are also provided. The spray pump unit consists of a nasal spray pump fitted with a blue safety clip and a blue plastic dust cover.

The Astelin® (azelastine hydrochloride) Nasal Spray, 137 mcg, bottle contains 30 mg (1 mg/mL) of azelastine hydrochloride. The bottle can deliver 200 metered sprays. Each spray delivers a mean of 0.137 mL solution containing 137 mcg of azelastine hydrochloride.

Storage: Store at controlled room temperature 20°-25°C (68°-77°F). Protect from freezing.

U.S. Patents 5,164,194; D447,419.

PATIENT: How To Use Instructions

FOR INTRANASAL USE ONLY

IMPORTANT: FOLLOW INSTRUCTIONS CAREFULLY TO ENSURE PROPER DOSING.

DOSING: The dosage of Astelin® Nasal Spray is 1 spray per nostril twice daily for pediatric patients (ages 5-11 years) with seasonal allergic rhinitis. For patients age 12 and older with seasonal allergic rhinitis the dosage is one or two sprays per nostril twice daily. For patients age 12 and older with nonallergic vasomotor rhinitis the dosage is two sprays per nostril twice daily. Keep your head tilted downward when spraying. Alternate sprays between nostrils. Breathe gently to avoid drawing any medication into the throat.

Follow the instructions below to use your Astelin® Nasal Spray pump.

TO PRIME:

1. Remove and retain the blue spray tip dust cover and blue safety clip.
2. Prime for initial use by putting two fingers on the shoulders of the spray pump unit and place your thumb on the bottom of the bottle. Press upward with thumb, release, and repeat until a fine mist appears (4 sprays or less). Now your pump is primed and ready to use.
3. If the solution is delivered in a stream of liquid, it may fail to provide maximum benefit and cause some discomfort. A fine mist can be produced only by a rapid and firm pumping action.
4. When 3 or more days have elapsed since the last use, the pump should be reprimed with 2 sprays or until a fine mist appears.

TO USE:

1. Gently blow nose to clear nostrils.
2. Keep your head tilted downward toward your toes.
3. Place the spray tip ¼ to ½ inch into one nostril. Hold bottle vertically upright (as shown), allowing spray tip to aim toward the back of the nose. Close other nostril with finger, rapidly press once with thumb and sniff gently at the same time. You may feel a brief burning or stinging sensation after using the unit.
4. Repeat in other nostril.
5. For patients aged 12 and over who were instructed by their doctor to administer 2 sprays in each nostril, repeat Steps 2 and 3 for second spray, again alternating sprays between nostrils.
6. Breathe in gently, and do not tilt head back after dosing to avoid drawing medication into the throat (where it will be tasted).

CAUTION: In case of accidental ingestion by a young child, seek professional assistance or contact a poison control center immediately. Do not spray in eyes.

NOTE: Keep the dust cover and safety clip on the spray pump unit when not in use. After each use and before replacing the dust cover, wipe the spray tip with a clean tissue or cloth.

FOR ASSISTANCE,
CALL 1-800-598-4856

TO CLEAN:

1. If spray nozzle becomes clogged, DO NOT ATTEMPT TO CLEAR IT USING A POINTED OBJECT. Remove the spray pump unit from the bottle.
2. Soak only the spray pump unit in warm water. Squirt several times while holding under water.
3. Make sure the spray pump unit is dry.
4. Reinsert the pump into the open bottle and tighten by turning clockwise.
5. To avoid leakage, firm pressure is required to ensure that the pump is fully threaded onto the bottle.
6. Follow instructions for priming.

Keep bottle tightly closed and away from children.

www.astelin.com

Manufactured by

Meda Pharmaceuticals

Meda Pharmaceuticals Inc.

Somerset, New Jersey 08873-4120

To report SUSPECTED ADVERSE REACTIONS, contact Meda Pharmaceuticals Inc. at 1-800-526-3840 or FDA at 1-800-FDA-1088 or www.fda.gov/medwatch.

©2009 Meda Pharmaceuticals Inc.

IN-023S6-07 Rev. 1/09

Relabeling of "Additional Barcode Label" by:
Physicians Total Care, Inc.
Tulsa, OK 74146

Package Label - Principal Display Panel – 30 mL Carton

30 mL
Astelin Nasal Spray 137 mcg®
(azelastine HCl)

Patient: See the Enclosed How
to Use Instructions
Antihistamine Nasal Spray

200 Metered Spray Dispensing
Package

FOR INTRANASAL USE ONLY
DO NOT SPRAY IN EYES

Each spray delivers 0.137 mL
(137 mcg azelastine hydrochloride).

Rx Only

Keep bottle tightly closed and away from children.